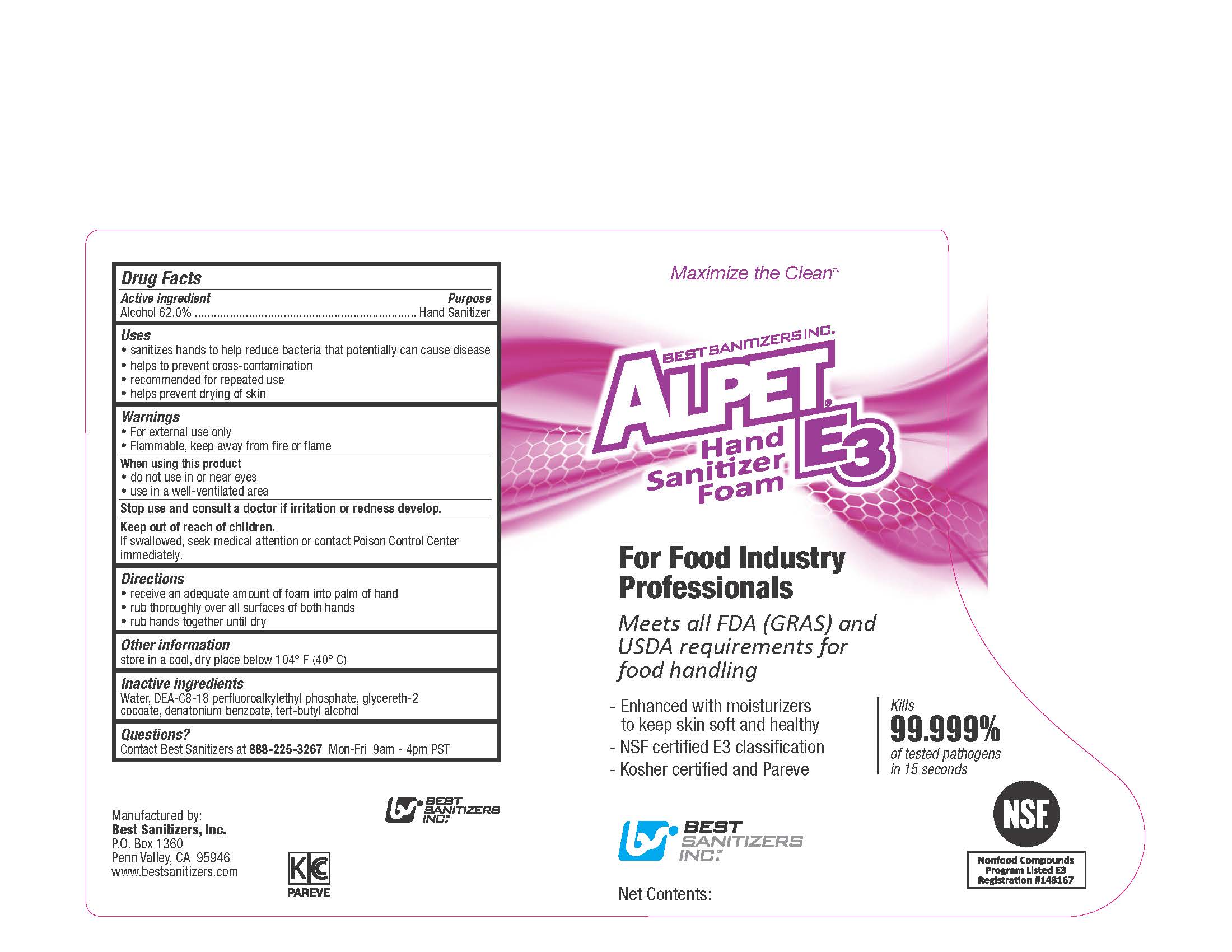 DRUG LABEL: ALPET E3 HAND SANITIZER FOAM
NDC: 59900-125 | Form: LIQUID
Manufacturer: Best Sanitizers, Inc.
Category: otc | Type: HUMAN OTC DRUG LABEL
Date: 20241205

ACTIVE INGREDIENTS: ALCOHOL 62 mL/100 mL
INACTIVE INGREDIENTS: WATER; DIETHANOLAMINE BIS(C8-C18 PERFLUOROALKYLETHYL)PHOSPHATE; GLYCERETH-2 COCOATE; DENATONIUM BENZOATE; TERT-BUTYL ALCOHOL

Drug Facts 5900-125

Active ingredient

Alcohol 62.0%

Purpose

Hand Sanitizer

Uses

- sanitizes hands to help reduce bacteria that potentially can cause disease

- helps to prevent cross-contamination

- recommended for repeated use

- helps prevent drying of skin

Warnings

- For external use only

- Flammable, keep away from fire or flame

When using this product

- do not use in or near eyes

- use in a well-ventilated area

Stop use and consult a doctor if irritation or redness develop.

Keep out of reach of children.

If swallowed, seek medical attention or contact Poison Control Center immediately

Directions

- receive an adequate amount of foam into palm of hand

- rub thoroughly over all surfaces of both hands

- rub hands together until dry

Other Information

store in a cool, dry place below 104oF (40oC)

Inactive Ingredients

Water, DEA-C8-18 perfluoroalkylethyl phosphate, glycereth-2 cocoate, denatonium benzoate, tert-butyl alcohol

Questions?

Contact Best Sanitizers at 888-225-3267Mon-Fri 9am - 4 pm PST

PACKAGE LABEL

Maximize the Clean

BEST SANITIZERS INC.

ALPET E3

Hand Sanitizer Foam

For Food Industry

Professionals

Meets all FDA (GRAS) and

USDA requirements for

food handling

Enhanced with moisturizers

to keep skin soft and healthy

NSF certified E3 classification

Kosher certified and Pareve

Kills

99.999%

of tested pathogens

in 15 seconds

BEST

SANITIZERS

INC.

NSF

Nonfood Compounds

Program Listed E3

Registration Number143167

Net Contents: